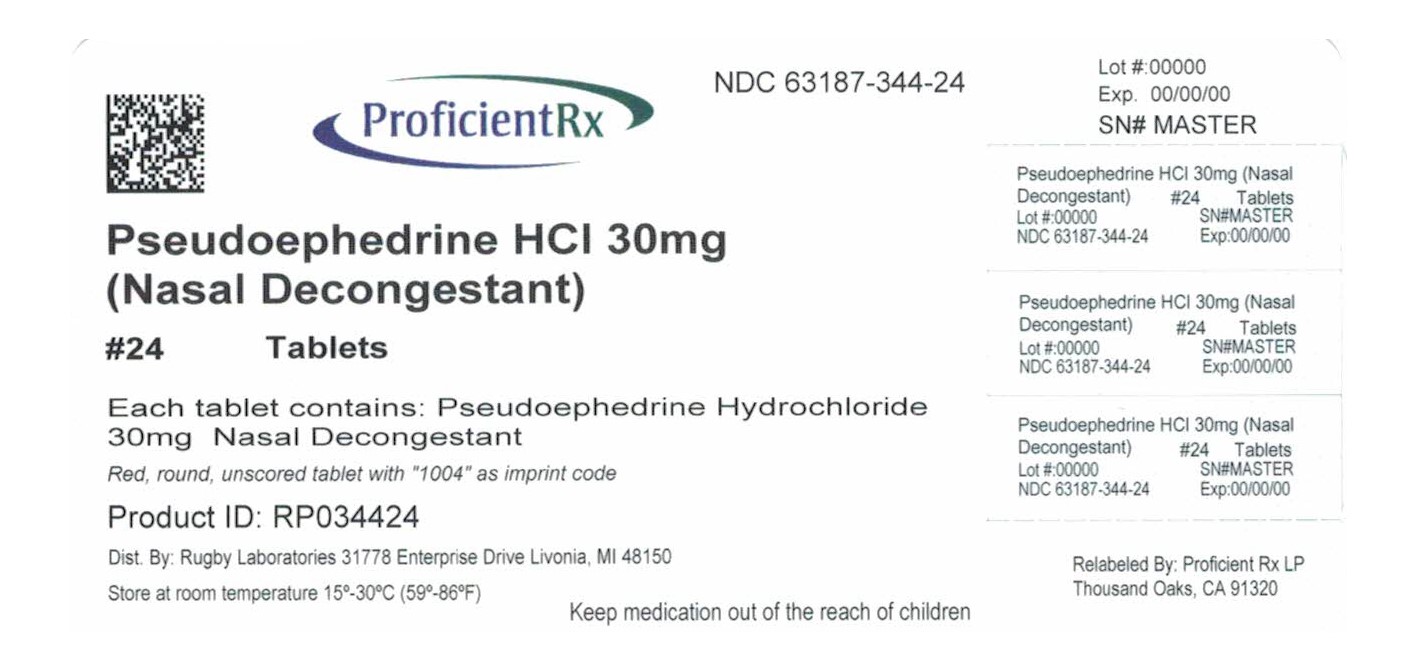 DRUG LABEL: Nasal Decongestant
NDC: 63187-344 | Form: TABLET
Manufacturer: Proficient Rx LP
Category: otc | Type: HUMAN OTC DRUG LABEL
Date: 20241001

ACTIVE INGREDIENTS: PSEUDOEPHEDRINE HYDROCHLORIDE 30 mg/1 1
INACTIVE INGREDIENTS: CROSCARMELLOSE SODIUM; FD&C YELLOW NO. 6; MAGNESIUM STEARATE; MICROCRYSTALLINE CELLULOSE; TITANIUM DIOXIDE; CALCIUM SULFATE, UNSPECIFIED FORM; CARNAUBA WAX; FD&C RED NO. 40; GELATIN, UNSPECIFIED; KAOLIN; ANHYDROUS LACTOSE; MAGNESIUM SILICATE; SHELLAC; SILICON DIOXIDE; 12-HYDROXYSTEARIC ACID; ACER SACCHARUM POLLEN

Equaline 44-112

Active ingredient (in each tablet)

- Pseudoephedrine HCl 30 mg

Purpose

- Nasal Congestant

Use(s)

- temporarily relieves nasal congestion due to the common cold, hay fever or other upper respiratory allergies
- temporarily restores freer breathing through the nose

Warnings

Do not use

- if you are now taking a prescription monoamine oxidase inhibitor (MAOI) (certain drugs for depression, psychiatric or emotional conditions, or Parkinson's disease), or 2 weeks after stoppin the MAOI drug. If you do not know if your prescription drug contains and MAOI, ask a doctor or pharmacist before taking this product.

Ask a doctor before use if you have

- diabetes
- high blood pressure
- heart disease
- thyroid disease
- trouble urinating due to an enlarged prostate gland

When using this product

- do not use more than directed

Stop use and ask a doctor if

- nervousness, dizziness, or sleeplessness occur
- symptoms do not improve within 7 days or occur with fever

If pregnant or breast-feeding,

- ask a health professional before use.

Keep out of reach of children.

- In case of overdose, get medical help or contact a Poison Control Center right away (1-800-222-1222).

Directions

adults and children 12 years and older | take 2 tablets every 4 to 6 hours; do not take more than 8 tablets in 24 hours
children ages 6 to 12 years | take 1 tablet every 4 to 6 hours; do not take more than 4 tablets in 24 hours
children under 6 years | do not use

Other information

- store at room temperature 15º-30ºC (59º-86ºF)

Inactive ingredients

- calcium sulfate, carnauba wax, croscarmellose sodium, FD&C red #40 lake, FD&C yellow #6 lake, gelatin, kaolin, lactose, magnesium silicate, magnesium stearate, microcrystalline cellulose, pharmaceutical glaze, silica, stearic acid, sugar and titanium dioxide

Questions or comments?

1-800-645-2158

Principal Display Panel

Rugby®

compare to Sudafed®

Decongestant active ingredient*

NDC 63187-344-24

Nasal Decongestant

pseudoephedrine HCl 30 mg

Temporarily relieves:

• nasal congestion due to cold & allergies withoout drowsiness

24 tablets, 30 mg each

TAMPER EVIDENT: SAFETY SEALED: DO NOT USE IF BLISTER SEAL IS BROKEN

Rev 04/13

R-29

DISTRIBUTED BY:
Rugby Laboratories
31778 Enterprise Drive
Livonia, MI 48150
Error! Hyperlink reference not valid.

Repackaged by:
Proficient Rx LP
Thousand Oaks, CA 91320